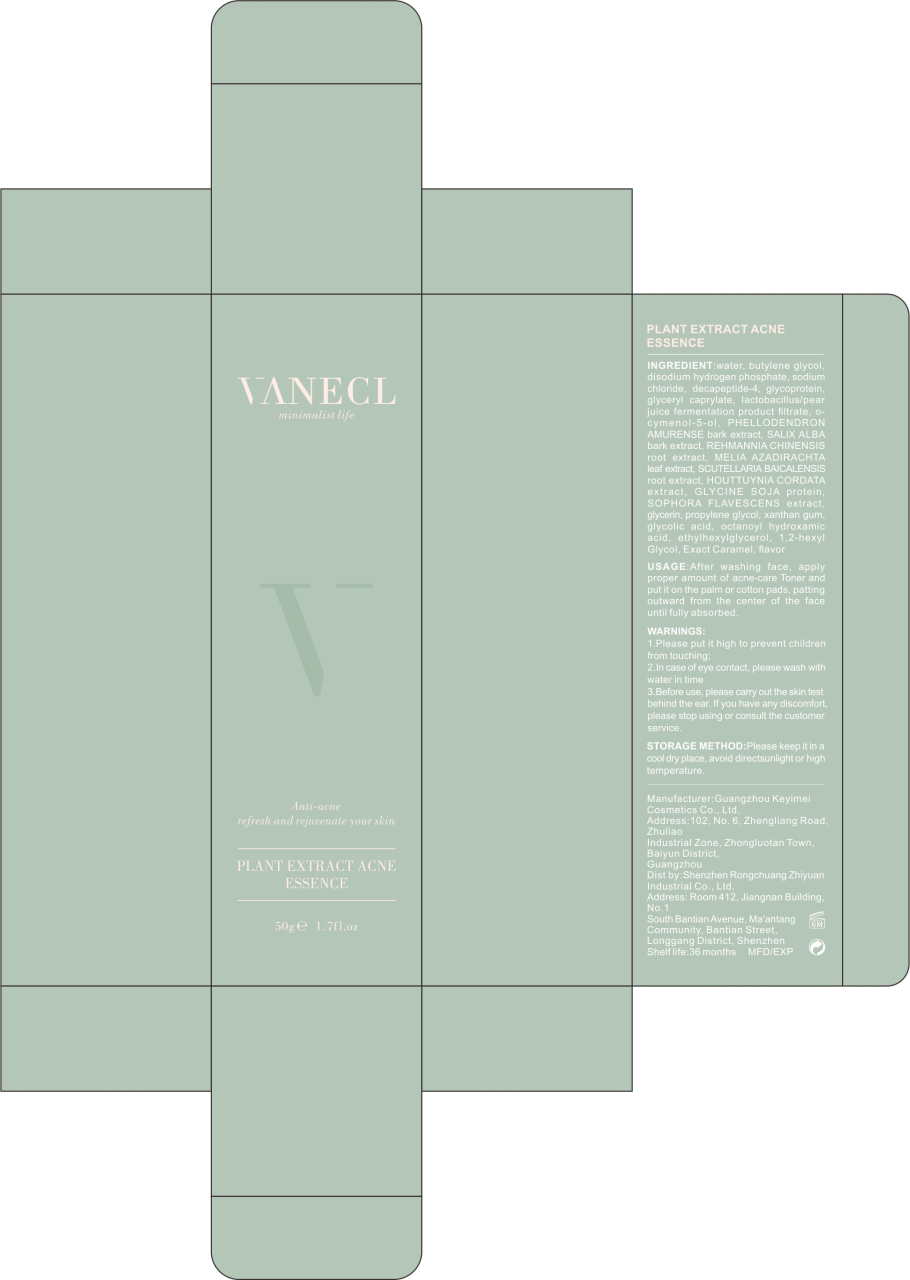 DRUG LABEL: Acne Control Essence
NDC: 80377-012 | Form: CREAM
Manufacturer: Shenzhen Rongchuang Zhiyuan Industrial Co., Ltd.
Category: otc | Type: HUMAN OTC DRUG LABEL
Date: 20200903

ACTIVE INGREDIENTS: ZINC OXIDE 5 g/100 g; REHMANNIA GLUTINOSA ROOT 2 g/100 g; SCUTELLARIA BAICALENSIS ROOT 2 g/100 g; OCTINOXATE 5 g/100 g
INACTIVE INGREDIENTS: CAPRYLHYDROXAMIC ACID; ETHYLHEXYLGLYCERIN; WATER; GLYCERIN; BUTYLENE GLYCOL; XANTHAN GUM; MELIA AZEDARACH LEAF; GLYCERYL CAPRYLATE; 1,2-HEXANEDIOL; GLYCOLIC ACID

PACKAGE LABEL

50g a bottle DNC: 80377-012-01